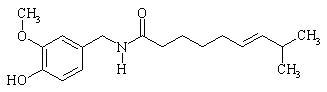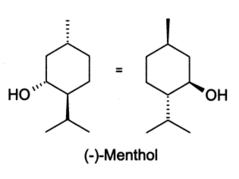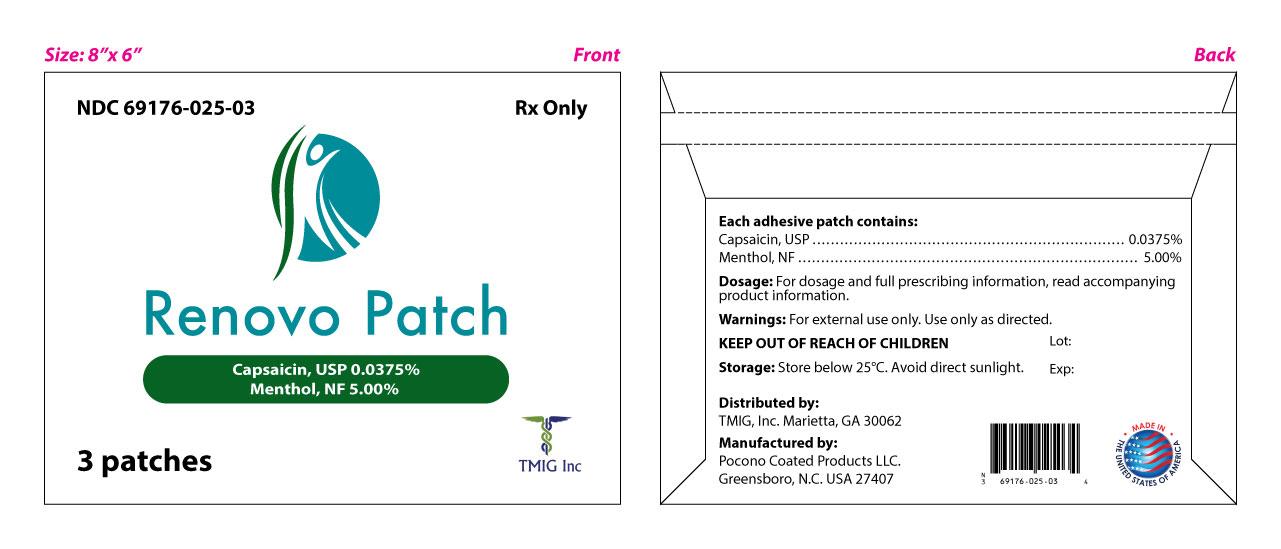 DRUG LABEL: Renovo
NDC: 69176-025 | Form: PATCH
Manufacturer: TMIG, Inc.
Category: prescription | Type: HUMAN PRESCRIPTION DRUG LABEL
Date: 20150126

ACTIVE INGREDIENTS: MENTHOL 5 g/100 g; CAPSAICIN 0.0375 g/100 g
INACTIVE INGREDIENTS: ALOE VERA LEAF; DIAZOLIDINYL UREA; EDETATE DISODIUM; GLYCERIN; IODOPROPYNYL BUTYLCARBAMATE; METHYLPARABEN; POLYSORBATE 80; PROPYLPARABEN; SODIUM POLYACRYLATE (2500000 MW); WATER

Renovo Patch

DESCRIPTION

Renovo Patch contains capsaicin and menthol in a localized dermal delivery system. The capsaicin in Renovo is a synthetic equivalent of the naturally occurring compound found in chili peppers. Capsaicin is soluble in alcohol, acetone, and ethyl acetate and very slightly soluble in water. The menthol is slightly soluble in water.

Renovo is a single-use patch stored in a foil pouch. Each Renovo patch is 8.3 cm x 12.5 cm (104 cm^2) and consists of a polyester backing film coated with a drug-containing silicone adhesive mixture, and covered with a removable polyester release liner.

The empirical formula for capsaicin is C18H27NO3, with a molecular weight of 305.42. The chemical compound capsaicin [(E)-8-methyl-N-vanillyl-6-nonenamide] is an activating ligand for transient receptor potential vanilloid 1 receptor (TRPV1) and it has the following structure:

The empirical formula for menthol is C10H20O, with a molecular weight of 156.27. The chemical compound menthol [(1R,2S,5R)-2-isopropyl-5-methylcyclohexanol ] is an activating ligand for transient receptor potential cation channel subfamily M member 8 (TRPM8). It has the following structure:

Each Relovo Patch contains 0.0375% capsaicin (0.0375 grams of capsaicin per patch) and 5.00% menthol (5 grams of menthol per patch). The Renovo patch contains the following inactive ingredients: Aloe Barbadensis Leaf (Aloe Vera Gel) Juice, Diazolidinyl Urea, EDTA Disodiumm Salt, Glycerin, Iodoproynyl Butylcabamate, Methylparaben, Polysorbate 80, Propylparaben, Sodium Polyacrylate, and Water.

INDICATIONS AND USAGE

Renovo Patch is indicated for the temporary relief of minor aches and muscle pains associated with arthritis, simple backache, strains, muscle soreness and stiffness.

Renovo Patch is an external analgesic/counterirritant.

CONTRAINDICATIONS

Renovo Patch is contraindicated for those patients with a history of hypersensitivity to any of the components of the preparation.

WARNINGS

- For external use only.
- Use only as directed.
- Avoid contact with eyes and mucous membranes.
- Do not cover with bandage.
- Do not use on wounds or damaged skin.
- Consult physician for children under 12.
- Do not use if you are allergic to Menthol.
- Stop use and ask a doctor if conditions worsen, symptoms persist for more than 7 days or clear up and occur again within a few days or rash, itching or excessive skin irritation occurs.
- KEEP OUT OF REACH OF CHILDREN.

DOSAGE AND ADMINISTRATION

Renovo patch contains 0.0375% capsaicin and 5.00% menthol.

Instructions for Use

- Clean and dry affected area
- Cut open pouch and remove patch
- Remove protective film and apply directly to area of pain
- Apply to affected area not more than 3 times daily
- Wash hands with soap after applying patch
- Reseal pouch containing unused patches

Directions

Adults and children 12 years and over | - apply to affected area - change patch 1 to 2 times daily
Children under 12 years | - consult physician before use

HOW SUPPLIED

Renovo Patch is supplied in cartons with either 1 re-sealable pouch containing 3 patches or 3 re-sealable pouches each containing 5 patches.

NDC 69176-025-03 3 Patches per carton

NDC 69176-025-15 15 Patches per carton

Storage: Store below 25°C. Avoid direct sunlight.

Distributed by:
TMIG, Inc., Marietta, GA 30062
770-579-8883

Manufactured by:
Pocono Coated Products, LLC
Greensboro, N.C. USA 27407